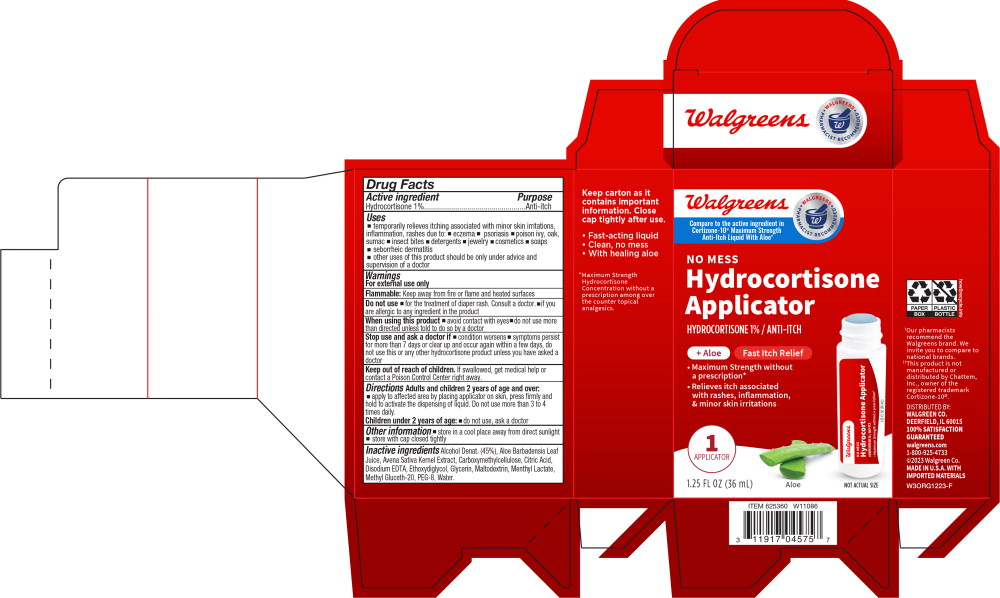 DRUG LABEL: No Mess Hydrocortisone Applicator
NDC: 0363-0358 | Form: LIQUID
Manufacturer: Walgreen Co.
Category: otc | Type: HUMAN OTC DRUG LABEL
Date: 20240216

ACTIVE INGREDIENTS: HYDROCORTISONE 10 mg/1 mL
INACTIVE INGREDIENTS: ALCOHOL; ALOE VERA LEAF; OAT; CARBOXYMETHYLCELLULOSE SODIUM, UNSPECIFIED; CITRIC ACID MONOHYDRATE; EDETATE DISODIUM; DIETHYLENE GLYCOL MONOETHYL ETHER; GLYCERIN; MALTODEXTRIN; MENTHYL LACTATE, (-)-; METHYL GLUCETH-20; POLYETHYLENE GLYCOL 400; WATER

Drug Facts

Active ingredient

Hydrocortisone 1%

Purpose

Anti-itch

Uses

- temporarily relieves itching associated with minor skin irritations, inflammation, rashes due to:
  - eczema
  - psoriasis
  - poison ivy, oak, sumac
  - insect bites
  - detergents
  - jewelry
  - cosmetics
  - soaps
- seborrheic dermatitis
- other uses of this product should be only under advice and supervision of a doctor

Warnings

For external use only

Flammable: Keep away from fire or flame and heated surfaces

Do not use

- for the treatment of diaper rash. Consult a doctor.
- if you are allergic to any ingredient in the product

When using this product

- avoid contact with eyes
- do not use more than directed unless told to do so by a doctor

Stop use and ask a doctor if

- condition worsens
- symptoms persist for more than 7 days or clear up and occur again within a few days, do not use this or any other hydrocortisone product unless you have asked a doctor

Keep out of reach of children. If swallowed, get medical help or contact a Poison Control Center right away.

Directions

Adults and children 2 years of age and over:

- apply to affected area by placing applicator on skin, press firmly and hold to activate the dispensing of liquid. Do not use more than 3 to 4 times daily.

Children under 2 years of age: do not use, ask a doctor

Other information

store in a cool place away from direct sunlight store with cap closed tightly

Inactive ingredients

Alcohol Denat. (45%), Aloe Barbadensis Leaf Juice, Avena Sativa Kernel Extract, Carboxymethylcellulose, Citric Acid, Disodium EDTA, Ethoxydiglycol, Glycerin, Maltodextrin, Menthyl Lactate, Methyl Gluceth-20, PEG-8, Water.

Principal Display Panel – 36 mL Carton Label

Walgreens

WALGREENS • PHARMACIST RECOMMENDED

Compare to the active ingredient in
Cortizone-10® Maximum Strength
Anti-Itch Liquid With Aloe††

NO MESS

Hydrocortisone
Applicator

HYDROCORTISONE 1% / ANTI-ITCH

+ Aloe

Fast Itch Relief

- Maximum Strength without
  a prescription*
- Relieves itch associated
  with rashes, inflammation,
  & minor skin irritations

1
APPLICATOR

1.25 FL OZ (36 mL)

Aloe

NOT ACTUAL SIZE